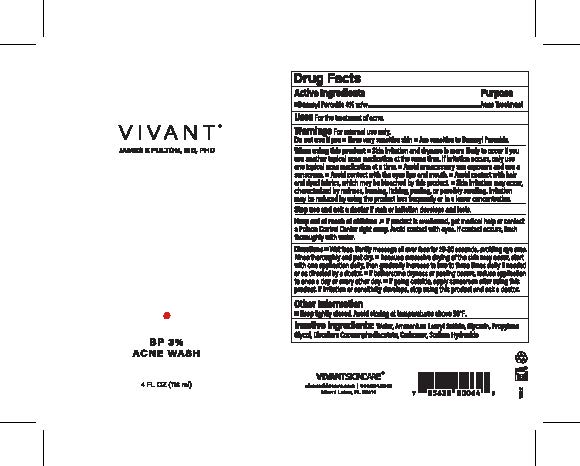 DRUG LABEL: Vivant BP3% Acne Wash
NDC: 63750-004 | Form: LIQUID
Manufacturer: Vivant Pharmaceuticals, LLC
Category: otc | Type: HUMAN OTC DRUG LABEL
Date: 20241105

ACTIVE INGREDIENTS: BENZOYL PEROXIDE 3 g/1 mL
INACTIVE INGREDIENTS: CARBOMER HOMOPOLYMER, UNSPECIFIED TYPE; AMMONIUM LAURYL SULFATE; DISODIUM COCOAMPHODIACETATE; WATER; GLYCERIN; PROPYLENE GLYCOL; SODIUM HYDROXIDE

Vivant BP3% Acne Wash

Active ingredient

Benzoyl peroxide 3%

Purpose

Acne treatment

Use

for the treatment of acne

Warnings

For external use only

Do not use

if you

• have very sensitive skin
• are sensitive to benzoyl peroxide

When using this product

- skin irritation and dryness is more likely to occur if you use another topical acne medication at the same time. If irritation occurs, only use one topical acne medication at a time.
- avoid unnecessary sun exposure and use a sunscreen
- avoid contact with the eyes, lips, and mouth
- avoid contact with hair and dyed fabrics, which may be bleached by this product
- skin irritation may occur, characterized by redness, burning, itching, peeling or possibly swelling. Irritation may be reduced by using the product less frequently or in a lower concentration.

Stop use and ask a doctor if

if rash or irritation develops an last

Keep out of reach of children.

If a product is swallowed, get medical help or contact a Poison Control Center right away. Avoid contact with eyes. If contact occurs, flus thoroughly with water.

Directions

Directions ■ Wet face. Gently massage all over face for 20-30 seconds, avoiding eye area.
Rinse thoroughly and pat dry. ■ Because excessive drying of the skin may occur, start with one application daily, then gradually increase to two to three times daily if needed or as directed by a doctor. ■ If bothersome dryness or peeling occurs, reduce application to once a day or every other day. ■ If going outside, apply sunscreen after using this product. If irritation or sensitivity develops, stop using this product and ask a doctor.

Inactive Ingredients

Inactive Ingredients: Water, Ammonium Lauryl Sulfate, Glycerin, Propylene Glycol, Disodium Cocoamphodiacetate, Carbomer, Sodium Hydroxide

Other Information

■ Keep tightly closed. Avoid storing at temperatures above 90°F.